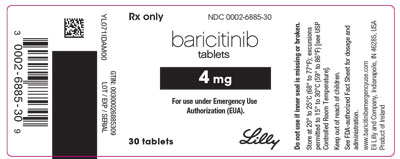 DRUG LABEL: Baricitinib
NDC: 0002-6885 | Form: TABLET, FILM COATED
Manufacturer: Eli Lilly and Company
Category: prescription | Type: HUMAN PRESCRIPTION DRUG LABEL
Date: 20220510

ACTIVE INGREDIENTS: baricitinib 4 mg/1 1
INACTIVE INGREDIENTS: Mannitol 50 mg/1 1; Cellulose, Microcrystalline 132 mg/1 1; Croscarmellose Sodium 12 mg/1 1; Magnesium Stearate 2 mg/1 1

BARICITINIB tablets, for oral use
Emergency Use Authorization

FACT SHEET FOR HEALTHCARE PROVIDERS
EMERGENCY USE AUTHORIZATION (EUA) OF BARICITINIB

The U.S. Food and Drug Administration (FDA) has issued an Emergency Use Authorization (EUA) to permit the emergency use of baricitinib for treatment of coronavirus disease 2019 (COVID-19) in hospitalized pediatric patients 2 to less than 18 years of age requiring supplemental oxygen, non-invasive or invasive mechanical ventilation, or extracorporeal membrane oxygenation (ECMO).

Baricitinib has been authorized by FDA for the emergency uses described above. Baricitinib is not FDA-approved for these uses.

Baricitinib is authorized only for the duration of the declaration that circumstances exist justifying the authorization of the emergency use of baricitinib under section 564(b)(1) of the Act, 21 U.S.C. § 360bbb-3(b)(1), unless the declaration is terminated or authorization revoked sooner.

This EUA is for the unapproved use of baricitinib to treat COVID-19 in hospitalized pediatric patients 2 to less than 18 years of age requiring supplemental oxygen, non-invasive or invasive mechanical ventilation, or ECMO.

Baricitinib is administered orally.

To request baricitinib under Emergency Use Authorization (EUA): In-patient pharmacies may order directly from an Authorized Distributor of Record. A current list of Lilly's Authorized Distributors of Record is available at www.lillytrade.com or visit www.baricitinibemergencyuse.com for additional access information.

The prescribing healthcare provider and/or the provider's designee is/are responsible for mandatory reporting of all serious adverse events and medication errors potentially related to baricitinib within 7 calendar days from the healthcare provider's awareness of the event.

See specific reporting instructions below.

The recommended dosage of baricitinib under the EUA is:

- Pediatric patients 9 years of age and older: 4 mg once daily
- Pediatric patients 2 years to less than 9 years of age: 2 mg once daily

Dosage modifications are recommended for laboratory abnormalities, including renal impairment (see Table 1).

The optimal duration of treatment is unknown.

The recommended total treatment duration of baricitinib is 14 days or until hospital discharge, whichever comes first.

For information on clinical trials that are testing the use of baricitinib in COVID-19, please see www.clinicaltrials.gov.

This Fact Sheet may be updated as new data become available. The most recent version of this Fact Sheet is available at www.baricitinibemergencyuse.com for download.

INSTRUCTIONS FOR ADMINISTRATION

This section provides essential information on the unapproved use of baricitinib to treat COVID-19 in hospitalized pediatric patients 2 to less than 18 years of age requiring supplemental oxygen, non-invasive or invasive mechanical ventilation, or ECMO under this EUA.

For more information, including pharmacokinetics and safety information of baricitinib, tradename Olumiant®, see the FDA-approved package insert at http://pi.lilly.com/us/olumiant-uspi.pdf.

Contraindications

There are no known contraindications for baricitinib.

Dosing

Patient Selection

- Evaluate baseline eGFR, liver enzymes, and complete blood count to determine treatment suitability and dose. Monitor closely patients with abnormal baseline and post-baseline laboratory values. See Table 1 for dosage modifications for patients with laboratory abnormalities.
- Baricitinib is not recommended for:
  - Patients who are on dialysis, have end-stage renal disease (ESRD, EGFR <15 mL/min/1.73 m^2), or have acute kidney injury
  - Patients with known active tuberculosis

Recommended Dosage for Pediatric Patients

Limited data informing baricitinib dosing in pediatric patients comes from ongoing clinical trials for other uses. Based on the available information, treatment for COVID-19 for pediatric patients under this EUA is as follows:

- The recommended dosage for patients 9 years of age and older is 4 mg once daily, with or without food, for 14 days of total treatment or until hospital discharge, whichever is first.
- The recommended dosage for patients ages 2 years through less than 9 years of age is 2 mg once daily, with or without food, for 14 days of total treatment or until hospital discharge, whichever is first.
- Baricitinib is not authorized for patients younger than 2 years of age.
- Dosage modifications in patients with renal or hepatic impairment are recommended (see Renal Impairment, Hepatic Impairment).

Table 1: Dosage Modifications
Dosage Modifications for Patients with Abnormal Laboratory Valuesa, b
Laboratory Analyte | Laboratory Analyte Value | Recommendation
eGFR | 60 - <90 mL/min/1.73 m^2 | - Pediatric patients 9 years of age and older: 4 mg once daily - Pediatric patients 2 years to less than 9 years of age: 2 mg once daily
eGFR | 30 - <60 mL/min/1.73 m^2 | - Pediatric patients 9 years of age and older: 2 mg once daily - Pediatric patients 2 years to less than 9 years of age: 1 mgc once daily
eGFR | 15 - <30 mL/min/1.73 m^2 | - Pediatric patients 9 years of age and older: 1 mgc once daily - Pediatric patients 2 years to less than 9 years of age: Not recommended
eGFR | <15 mL/min/1.73 m^2 | Not recommended
Absolute Lymphocyte Count (ALC) | ≥200 cells/μL | Maintain dose
Absolute Lymphocyte Count (ALC) | <200 cells/μL | Consider interruption until ALC is ≥200 cells/μL
Absolute Neutrophil Count (ANC) | ≥500 cells/μL | Maintain dose
Absolute Neutrophil Count (ANC) | <500 cells/μL | Consider interruption until ANC is ≥500 cells/μL
Aminotransferases | If increases in ALT or AST are observed and drug-induced liver injury (DILI) is suspected | Interrupt baricitinib until the diagnosis of DILI is excluded
Dosage Modifications when Coadministered with Other Medications
Concomitant Medication |  | Recommendation
Strong OAT3 Inhibitors (e.g., probenecid) |  | - If the recommended baricitinib dose is 4 mg once daily, reduce dose to 2 mg once daily. - If the recommended baricitinib dose is 2 mg once daily, reduce dose to 1 mgc once daily. - If the recommended baricitinib dose is 1 mg once daily, consider discontinuing probenecid.
a Abbreviations: ALC = absolute lymphocyte count, ALT = alanine transaminase, ANC = absolute neutrophil count, AST = aspartate transaminase, DILI = drug induced liver injury, eGFR = estimated glomerular filtration rate.
b If a laboratory abnormality is likely due to the underlying disease state, consider the risks and benefits of continuing baricitinib at the same or a reduced dose.
c Only if a 1 mg tablet is not available, a 2 mg tablet can be split using a tablet splitter that has a razor blade to administer half a 2 mg tablet once daily. The tablet should be split along the longest diameter. If the portions of the tablet are determined to be visually unequal they should be discarded. Take care in storing the second tablet half to avoid breakage prior to next dose.

Pregnancy

Baricitinib should be used during pregnancy only if the potential benefit justifies the potential risk for the mother and the fetus. Consistent with the mechanism of action, embryo-fetal toxicities including skeletal anomalies and reduced fertility have been observed in animals dosed in excess of the maximum human exposure. The limited human data on use of baricitinib in pregnant women are not sufficient to inform a drug-associated risk for major birth defects or miscarriage.

See also Section 8.1 Pregnancy in the FDA approved full prescribing information for more information.

Renal Impairment

There are limited data for baricitinib in patients with severe renal impairment:

- Baricitinib is not recommended for patients who are on dialysis, have ESRD, or have acute kidney injury.
- See Table 1 for treatment modifications for patients with laboratory abnormalities:
  - Baricitinib should only be used in pediatric patients 9 years of age and older with eGFR 15 to <30 mL/min/1.73 m^2 if the potential benefit outweighs the potential risk.
  - Baricitinib is not recommended for pediatric patients ages 2 years through less than 9 years of age with eGFR <30 mL/min/1.73 m^2.

Hepatic Impairment

Baricitinib has not been studied in patients with severe hepatic impairment. Baricitinib should only be used in patients with severe hepatic impairment if the potential benefit outweighs the potential risk. It is not known if dosage modification is needed in patients with severe hepatic impairment.

See Table 1 for dosage modifications for patients with abnormal laboratory values.

Administration

Baricitinib tablets are given orally once daily; with or without food.

Alternative Administration for Patients Unable to Swallow Tablets

For patients who are unable to swallow whole tablets, an alternative mode of administration may be considered:

- Oral dispersion
- Gastrostomy tube (G tube)
- Nasogastric tube (NG tube) or orogastric tube (OG tube)

Intact tablets are not hazardous. Tablets may be crushed to facilitate dispersion. It is not known if powder from the crushed tablets may constitute a reproductive hazard to the preparer. Use proper control measures (e.g., ventilated enclosure) or personal protective equipment (i.e., N95 respirator).

Dispersed tablets are stable in water for up to 4 hours.

Preparation Instructions for Alternative Administration

- Oral administration of dispersed tablets in water:
  For patients who are unable to swallow whole tablets, 1-mg, 2-mg, or 4-mg baricitinib tablet(s), or any combination of tablets necessary to achieve the desired dose up to 4-mg may be placed in a container with approximately 10 mL (5 mL minimum) of room temperature water, dispersed by gently swirling the tablet(s) and immediately taken orally. The container should be rinsed with an additional 10 mL (5 mL minimum) of room temperature water and the entire contents swallowed by the patient (Table 2).
- Administration via G tube:
  For patients with a G tube, 1-mg, 2-mg, or 4-mg baricitinib tablet(s), or any combination of tablets necessary to achieve the desired dose up to 4-mg may be placed in a container with approximately 15 mL (10 mL minimum) of room temperature water and dispersed with gentle swirling. Ensure the tablet(s) are sufficiently dispersed to allow free passage through the tip of the syringe. Withdraw entire contents from the container into an appropriate syringe and immediately administer through the gastric feeding tube. Rinse container with approximately 15 mL (10 mL minimum) of room temperature water, withdraw the contents into the syringe, and administer through the tube (Table 2).
- Administration via NG or OG tube:
  For patients with an NG or OG tube, 1-mg, 2-mg, or 4-mg baricitinib tablet(s), or a combination of tablets necessary to achieve the desired dose up to 4-mg may be placed into a container with approximately 30 mL of room temperature water and dispersed with gentle swirling. Ensure the tablet(s) are sufficiently dispersed to allow free passage through the tip of the syringe. Withdraw the entire contents from the container into an appropriate syringe and immediately administer through the enteral feeding tube. To avoid clogging of small diameter tubes (smaller than 12 Fr), the syringe can be held horizontally and shaken during administration. Rinse container with a sufficient amount (minimum of 15 mL) of room temperature water, withdraw the contents into the syringe, and administer through the tube (Table 2).

Table 2: Dispersion and Rinse Volume for Alternative Administration
Administration via | Dispersion Volume | Container Rinse Volume
Oral dispersion | 10 mL | 10 mL
G tube | 15 mL | 15 mL
NG or OG tube | 30 mL | 15 mL

Drug Interactions

Strong OAT3 Inhibitors: Baricitinib exposure is increased when baricitinib is co-administered with strong OAT3 inhibitors (such as probenecid). See Table 1 for dosage modifications for patients taking strong OAT3 inhibitors, such as probenecid.

Other JAK Inhibitors or biologic disease modifying anti-rheumatic drugs (DMARDs): Baricitinib has not been studied in combination with other JAK inhibitors or with biologic DMARDs (biologic treatments targeting cytokines, B-cells, or T-cells) and is not recommended.

Pharmacology

Pharmacokinetics: The pharmacokinetics (PK) in adult patients with COVID-19 who are intubated and have baricitinib administered via NG tube is similar to that in healthy adult subjects. The half-life of baricitinib in healthy subjects is approximately 10 hours.

The PK of baricitinib in pediatric patients with COVID-19 has not been evaluated.

Based on an analysis of interim PK data from ongoing clinicals of baricitinib in other pediatric chronic autoimmune disorders, the recommended dosing regimen is expected to result in comparable steady-state plasma exposures of baricitinib in pediatric patients 2 to less than 18 years of age as observed in healthy adults.

Warnings

There are limited clinical data available for baricitinib in pediatric patients 2 to less than 18 years of age hospitalized with COVID-19 requiring supplemental oxygen, non-invasive or invasive mechanical ventilation, or ECMO.

Serious Infections

There is limited information regarding use of baricitinib in patients with COVID-19 and concomitant active serious infections.

Serious infections, including viral reactivation, have occurred in patients with COVID-19 receiving baricitinib:

- Avoid the use of baricitinib with known active tuberculosis.
- Consider if the potential benefits outweigh the potential risks of baricitinib treatment in patients with active serious infections other than COVID-19 or chronic / recurrent infections.

Thrombosis

Serious venous thrombosis, including pulmonary embolism have been observed in COVID-19 patients treated with baricitinib and are known adverse drug reactions of baricitinib. If clinical features of deep vein thrombosis/pulmonary embolism occur, patients should be evaluated promptly and treated appropriately.

Abnormal Laboratory Values

There is limited information regarding use of baricitinib in patients with COVID-19 and any of the following clinical findings:

- ANC <1000 cells/mm^3
- ALC <200 cells/mm^3
- Hemoglobin <8 g/dL

Evaluate at baseline and thereafter according to local patient management practice. Monitor closely when treating patients with abnormal baseline and post-baseline laboratory values.

See Table 1 for dosage modifications for patients with abnormal renal, hematological and hepatic laboratory values. Manage patients according to routine clinical guidelines.

Vaccinations

Avoid use of live vaccines with baricitinib.

Hypersensitivity

If a serious hypersensitivity occurs, discontinue baricitinib while evaluating the potential causes of the reaction.

See Warnings and Precautions in the FDA approved full prescribing information for additional information on risks associated with baricitinib treatment.

Serious Side Effects

Serious venous thrombosis, including pulmonary embolism, and serious infections have been observed in COVID-19 patients treated with baricitinib and are known adverse drug reactions of baricitinib.

Scientific Evidence Supporting This EUA

Baricitinib is being studied in an ongoing clinical trial in pediatric patients hospitalized with COVID-19 requiring supplemental oxygen, non-invasive or invasive mechanical ventilation, or ECMO. Use in this age group is based on extrapolation of pediatric efficacy from the adequate and well-controlled studies in adults, ACTT-2 and COV-BARRIER, and safety data from ongoing clinical trials of baricitinib in other pediatric conditions.

The efficacy and safety of baricitinib were assessed in 2 Phase 3, randomized, double-blind, placebo-controlled clinical trials:

- COVID I (ACTT-2, NCT04401579) which evaluated the combination of baricitinib 4 mg + remdesivir compared to placebo + remdesivir.
- COVID II (COV-BARRIER, NCT04421027), which evaluated baricitinib 4 mg compared to placebo. Patients could remain on background therapy, as defined per local guidelines. An additional exploratory sub-study in patients requiring invasive mechanical ventilation or ECMO at baseline was also conducted under this protocol and analyzed separately.

Efficacy

COVID I

A randomized, double-blind, placebo-controlled clinical trial (NCT04401579) of hospitalized adults with confirmed SARS-CoV-2 infection compared treatment with baricitinib plus remdesivir (n=515) with placebo plus remdesivir (n=518). Patients had to have laboratory-confirmed SARS-CoV-2 infection as well as at least one of the following to be enrolled in the trial: radiographic infiltrates by imaging, SpO2 ≤94% on room air, a requirement for supplemental oxygen, or a requirement for mechanical ventilation or ECMO. Patients treated with the combination received the following regimen:

- Baricitinib 4 mg once daily (orally) for up to 14 days or until hospital discharge, whichever came first
- Remdesivir 200 mg on Day 1 and 100 mg once daily (via intravenous infusion) on subsequent days for a total treatment duration of 10 days or until hospital discharge

In this study prophylaxis for venous thromboembolic event (VTEs) was recommended for all patients unless a major contraindication was noted.

For the overall population (N=1033 patients) at randomization, mean age was 55 years (with 30% of patients aged 65 or older); 63% of patients were male, 51% were Hispanic or Latino, 48% were White, 15% were Black or African American, and 10% were Asian; 14% did not require supplemental oxygen, 55% required supplemental oxygen, 21% required non-invasive ventilation or high-flow oxygen, and 11% required invasive mechanical ventilation or ECMO. The most common comorbidities were obesity (56%), hypertension (52%), and type 2 diabetes (37%). Demographics and disease characteristics were balanced across the combination group and the placebo group.

The primary endpoint, for the intent to treat population, was time to recovery within 29 days after randomization. Recovery was defined as being discharged from the hospital without limitations on activities, being discharged from the hospital with limitations on activities and/or requiring home oxygen or hospitalized but not requiring supplemental oxygen and no longer requiring medical care. The key secondary endpoint was clinical status on Day 15 assessed on an 8-point ordinal scale (OS) consisting of the following categories:

1. Not hospitalized, no limitations on activities [OS-1];
2. Not hospitalized, limitation on activities and/or requiring home oxygen [OS-2];
3. Hospitalized, not requiring supplemental oxygen - no longer requires ongoing medical care [OS-3];
4. Hospitalized, not requiring supplemental oxygen - requiring ongoing medical care (COVID-19 related or otherwise) [OS 4];
5. Hospitalized, requiring supplemental oxygen [OS 5];
6. Hospitalized, on non-invasive ventilation or high-flow oxygen devices [OS 6];
7. Hospitalized, on invasive mechanical ventilation or ECMO [OS 7]; and
8. Death [OS 8]

For the overall population, the median time to recovery (defined as discharged from hospital or hospitalized but not requiring supplemental oxygen or ongoing medical care) was 7 days for baricitinib + remdesivir compared to 8 days for placebo + remdesivir [hazard ratio: 1.16 (95% CI 1.01, 1.33); p=0.035].

Patients assigned to baricitinib + remdesivir were more likely to have a better clinical status (according to an 8-point ordinal scale) at Day 15 compared to patients assigned to placebo + remdesivir [odds ratio: 1.26 (95% CI 1.01, 1.57); p=0.044].

The proportion of patients who died or progressed to non-invasive ventilation/high-flow oxygen or invasive mechanical ventilation by Day 29 was lower in baricitinib + remdesivir (23%) compared to placebo + remdesivir (28%) [odds ratio: 0.74 (95% CI 0.56, 0.99); p=0.039]. Patients who required non-invasive ventilation/high-flow oxygen or invasive mechanical ventilation (including ECMO) at baseline needed to worsen by at least 1 point on an 8-point ordinal scale to progress.

The proportion of patients who died by Day 29 was 4.7% (24/515) for baricitinib + remdesivir compared to 7.1% (37/518) for placebo + remdesivir [Kaplan Meier estimated difference in Day 29 probability of mortality: -2.6% (95% CI -5.8%, 0.5%); hazard ratio = 0.65 (95% CI: 0.39, 1.09)].

COVID II

A randomized, double-blind, placebo-controlled clinical trial (NCT04421027) of hospitalized adults with confirmed SARS-CoV-2 infection compared treatment with baricitinib 4mg once daily (n=764) with placebo (n=761) for 14 days or hospital discharge, whichever came first. Patients could remain on background standard of care, as defined per local guidelines, including antimalarials, antivirals, corticosteroids, and/or azithromycin. In this study prophylaxis for venous thromboembolic event (VTE) prophylaxis was required for all patients unless contraindicated.

The most frequently used therapies at baseline were:

- corticosteroids (79% of patients, mostly dexamethasone)
- remdesivir (19% of patients)

Patients had to have laboratory-confirmed SARS-CoV-2 infection, at least one instance of elevation in at least one inflammatory marker above the upper limit of normal according to local laboratory ranges (CRP, D-dimer, LDH, ferritin), and at least one of the following to be enrolled in the trial: radiographic infiltrates by imaging, SpO2 <94% on room air, evidence of active COVID infection (with clinical symptoms including any of the following: fever, vomiting, diarrhea, dry cough, tachypnea defined as respiratory rate >24 breaths/min) or requirement for supplemental oxygen.

For the overall population (N=1525 patients) at randomization, mean age was 58 years (with 33% of patients aged 65 or older); 63% of patients were male, 60% were White, 5% were Black or African American,11% were Asian; 12% did not require supplemental oxygen (OS 4), 63% required supplemental oxygen (OS 5), 24% required non-invasive ventilation or high-flow oxygen (OS 6). The most common comorbidities were hypertension (48%), obesity (33%), and type 2 diabetes (29%). Demographics and disease characteristics were balanced across the baricitinib and placebo groups.

The primary endpoint was the proportion of patients who died or progressed to non-invasive ventilation/high-flow oxygen or invasive mechanical ventilation within the first 28-days of the study. Patients who required non-invasive ventilation/high-flow oxygen at baseline needed to worsen by at least 1 point on an 8-point OS to progress (refer to the description of COVID I for the definition of the 8-point OS). A key secondary endpoint was all-cause mortality by Day 28.

The estimated proportion of patients who died or progressed to non-invasive ventilation/high-flow oxygen or invasive mechanical ventilation was lower in patients treated with baricitinib (27.8%) compared to placebo (30.5%), but this effect was not statistically significant [odds ratio: 0.85 (95% CI 0.67, 1.08); p=0.180].

The proportion of patients who died by Day 28 was 8.1% (62/764) for baricitinib compared to 13.3% (101/761) for placebo [estimated difference in Day 28 probability of mortality = -4.9% (95% CI: -8.0%, -1.9%); hazard ratio = 0.56 (95% CI: 0.41, 0.77)].

COVID II Exploratory Sub-Study

In a separate group of patients requiring invasive mechanical ventilation or ECMO at baseline and enrolled in an addendum to COVID II, a pre-specified exploratory analysis showed that the proportion who died by Day 28 was 39.2% (20/51) for baricitinib compared to 58.0% (29/50) for placebo [estimated difference in Day 28 risk of mortality = -18.8% (95% CI: -36.3%, 0.6%); hazard ratio = 0.54 (95% CI: 0.31, 0.96)].

Safety

The safety of baricitinib was evaluated in two randomized, placebo-controlled clinical trials of hospitalized adults with COVID-19 for up to 29 days, in which 1307 patients received at least one dose of baricitinib 4 mg once daily, and 1310 patients received placebo, for up to 14 days or hospital discharge, whichever occurred first. In these studies, prophylaxis for venous thromboembolic event (VTEs) was recommended or required for all patients unless a major contraindication was noted.

Overall, the safety profile observed in patients with COVID-19 treated with baricitinib was consistent with the safety profile in patients with rheumatoid arthritis.

Overall Infections – During the first 29 days of the randomized clinical trials, infections were reported in 194 patients (14.8%) treated with baricitinib 4 mg and by 219 patients (16.7%) treated with placebo. The most commonly reported infection with baricitinib was pneumonia (3.1%).

Serious Infections – During the first 29 days of the randomized clinical trials, serious infections were reported in 98 patients (7.5%) treated with baricitinib 4 mg and 120 patients (9.2%) treated with placebo. The most commonly reported serious infections with baricitinib were COVID-19 pneumonia (2.1%) and septic shock (2.1%).

Opportunistic Infections – During the first 29 days of the randomized clinical trials, opportunistic infections were reported in 12 patients (0.9%) treated with baricitinib 4 mg and 14 patients (1.1%) treated with placebo. Tuberculosis was reported in 1 patient (0.1%) treated with baricitinib 4 mg and 0 patients treated with placebo.

Venous Thrombosis Events - During the first 29 days of the randomized clinical trials, pulmonary embolism was reported in 20 patients (1.5%) treated with baricitinib 4 mg and 11 patients (0.8%) treated with placebo. Deep Vein Thrombosis was reported in 20 patients (1.5%) treated with baricitinib 4 mg and 18 patients (1.4%) treated with placebo.

Of the known adverse drug reactions of baricitinib in clinical trials of other indications, Table 3 summarizes the observed frequencies of adverse reactions occurring in ≥ 1% of patients during the first 29 days of studies COVID I and COVID II.

Table 3: Adverse Reactions That Occurred in Greater Than or Equal to 1% of Patients Treated with Baricitinib 4 mg Treated Patients During the First 29 Days in Placebo-Controlled Trials for COVID-19
 | Placebo N = 1310 n (%) | Baricitinib 4 mg N = 1307 n (%)
ALT ≥3 x ULNa | 201 (16.0) | 230 (18.1)
AST ≥3 x ULNa | 117 (9.4) | 149 (11.8)
Thrombocytosis >600,000 cells/mm3a | 34 (4.6) | 59 (7.9)
Creatine phosphokinase (CPK) >5 x ULNa, b | 38 (4.7) | 36 (4.5)
Neutropenia <1000 cells/mm3a | 22 (1.8) | 26 (2.2)
Deep vein thrombosis | 18 (1.4) | 20 (1.5)
Pulmonary embolism | 11 (0.8) | 20 (1.5)
Urinary tract infection | 13 (1.0) | 19 (1.5)
a As assessed by measured values within the clinical trial database. Frequencies are based on shifts from pre-treatment to post-treatment (with number at risk as the denominator), except for ALT and AST for which frequencies are based on observed elevation during treatment.
b Creatine phosphokinase frequencies presented in the table were available for a single trial (COVID II) in patients with COVID-19 and do not represent integrated data.

How Supplied/Storage and Handling

How Supplied

Baricitinib for oral administration is available as debossed, film-coated, immediate-release tablets. Each tablet contains a recessed area on each face of the tablet surface.

Under this EUA, baricitinib is supplied in 30 count bottles as follows:

- OLUMIANT (baricitinib) tablet 1 mg (NDC 0002-4732-30)
- OLUMIANT (baricitinib) tablet 2 mg (NDC 0002-4182-30), and
- OLUMIANT (baricitinib) tablet 4 mg (NDC 0002-4479-30)

Storage and Handling

Store at 20°C to 25°C (68°F to 77°F); excursions permitted to 15°C to 30°C (59°F to 86°F).

Keep out of reach of children.

Important Information for Patients, Parents and Caregivers

See Fact Sheets for Patients, Parents and Caregivers.

INSTRUCTIONS FOR HEALTHCARE PROVIDERS

As the healthcare provider, you must communicate to your patient or parent/caregiver, as age appropriate, information consistent with the “Fact Sheet for Patients, Parents and Caregivers” (and provide a copy of the Fact Sheet) prior to the patient receiving baricitinib, including:

- FDA has authorized the emergency use of baricitinib to treat COVID-19 in hospitalized pediatric patients 2 to less than 18 years of age requiring supplemental oxygen, non-invasive or invasive mechanical ventilation, or extracorporeal membrane oxygenation (ECMO). This is not an FDA-approved use of baricitinib.
- The patient or parent/caregiver has the option to accept or refuse baricitinib.
- The significant known and potential risks and benefits of baricitinib, and the extent to which such potential risks and benefits are unknown.
- Information on available alternative treatments and the risks and benefits of those alternatives, including clinical trials.

If providing this information will delay the administration of baricitinib to a degree that would endanger the lives of patients, the information must be provided to the patients as soon as practicable after baricitinib is administered.

For information on clinical trials that are testing the use of baricitinib for COVID-19, please see www.clinicaltrials.gov.

MANDATORY REQUIREMENTS FOR BARICITINIB ADMINISTRATION UNDER EMERGENCY USE AUTHORIZATION

In order to mitigate the risks of using this approved product for an unapproved use under EUA and to optimize the potential benefit of baricitinib, the following items are required. Use of baricitinib under this EUA is limited to the following (all requirements must be met):

1. Treatment of coronavirus disease 2019 (COVID-19) in hospitalized pediatric patients 2 to less than 18 years of age requiring supplemental oxygen, non-invasive or invasive mechanical ventilation, or ECMO.
2. As the healthcare provider, communicate to your patient or parent/caregiver information consistent with the “Fact Sheet for Patients, Parents and Caregivers” prior to the patient receiving baricitinib. Healthcare providers (to the extent practicable given the circumstances of the emergency) must document in the patient's medical record that the patient/caregiver has been:
  1. Given the “Fact Sheet for Patients, Parents and Caregivers”,
  2. Informed of alternatives to receiving authorized baricitinib, and
  3. Informed that baricitinib is an approved drug that is authorized for the unapproved use under this Emergency Use Authorization.
3. Patients must have an eGFR, aminotransferases, and CBC with differential determined prior to first administration of baricitinib.
4. The prescribing healthcare provider and/or the provider’s designee is/are responsible for mandatory reporting of all serious adverse events* and medication errors potentially related to baricitinib within 7 calendar days from the healthcare provider’s awareness of the event, using FDA Form 3500 (for information on how to access this form, see below). The FDA requires that such reports, using FDA Form 3500, include the following:
  - Patient demographics and baseline characteristics (e.g., patient identifier, age or date of birth, gender, weight, ethnicity, and race)
  - A statement "Baricitinib use for COVID-19 under Emergency Use Authorization (EUA)” under the “Describe Event, Problem, or Product Use/Medication Error” heading
  - Information about the serious adverse event or medication error (e.g., signs and symptoms, test/laboratory data, complications, timing of drug initiation in relation to the occurrence of the event, duration of the event, treatments required to mitigate the event, evidence of event improvement/disappearance after stopping or reducing the dosage, evidence of event reappearance after reintroduction, clinical outcomes).
  - Patient’s preexisting medical conditions and use of concomitant products
  - Information about the product (e.g., dosage, route of administration, NDC #).

Submit adverse event and medication error reports, using Form 3500, to FDA MedWatch using one of the following methods:

- Complete and submit the report online:
  www.fda.gov/medwatch/report.htm
- Complete and submit a postage-paid Form FDA 3500
  (https://www.fda.gov/media/76299/download) and return by:
  - Mail to MedWatch, 5600 Fishers Lane, Rockville, MD 20852-9787, or
  - Fax (1-800-FDA-0178), or
- Call 1-800-FDA-1088 to request a reporting form.

In addition, please provide a copy of all FDA MedWatch forms to:
Eli Lilly and Company, Global Patient Safety
Fax: 1-317-277-0853
E-mail: mailindata_gsmtindy@lilly.com
Or call Eli Lilly and Company at 1-855-LillyC19 (1-855-545-5921) to report adverse events.

The prescribing healthcare provider and/or the provider's designee is/are responsible for mandatory responses to requests from FDA for information about adverse events and medication errors following receipt of baricitinib.

*Serious Adverse Events are defined as:

- Death;
- A life-threatening adverse event;
- Inpatient hospitalization or prolongation of existing hospitalization;
- A persistent or significant incapacity or substantial disruption of the ability to conduct normal life functions;
- A congenital anomaly/birth defect;
- Other important medical event, which may require a medical or surgical intervention to prevent death, a life-threatening event, hospitalization, disability, or congenital anomaly.

APPROVED AVAILABLE ALTERNATIVES

Veklury (remdesivir) is FDA-approved for the treatment of COVID-19 in adults and pediatric patients (28 days of age and older and weighing at least 3 kg) with positive results of direct SARS-CoV-2 viral testing, who are hospitalized, or not hospitalized and have mild-to-moderate COVID-19, and are at high risk for progression to severe COVID-19, including hospitalization or death. Veklury is administered via intravenous infusion for a total treatment duration of 3-5 days. Although Veklury is an approved alternative treatment of COVID-19 in pediatric patients (28 days of age and older and weighing at least 3 kg) with positive results of direct SARS-COV-2 viral testing, who are hospitalized, FDA does not consider Veklury to be an adequate alternative to baricitinib for this authorized use. Veklury is a nucleoside ribonucleic acid polymerase inhibitor that has demonstrated antiviral activity against SARS-COV-2. Baricitinib is a Janus kinase (JAK) inhibitor, a class of drugs that block extracellular signals from multiple cytokines that are involved in inflammatory diseases and thought to contribute to inflammation and worsening of COVID-19. This is distinct from Veklury, which acts as an antiviral agent.

Additional information on COVID-19 treatments can be found at https://www.cdc.gov/coronavirus/2019-ncov/index.html. The healthcare provider should visit https://clinicaltrials.gov/ to determine whether the patient may be eligible for enrollment in a clinical trial.

JUSTIFICATION FOR EMERGENCY USE OF DRUGS DURING THE COVID-19 PANDEMIC

There is currently an outbreak of Coronavirus Disease 2019 (COVID-19) caused by SARS-CoV2, a novel coronavirus. The Secretary of HHS has declared that:

- A public health emergency related to COVID-19 has existed since January 27, 2020.
- Circumstances exist justifying the authorization of emergency use of drugs and biological products during the COVID-19 pandemic (March 27, 2020 declaration).

An EUA is a FDA authorization for the emergency use of an unapproved product or unapproved use of an approved product (i.e., drug, biological product, or device) in the United States under certain circumstances including, but not limited to, when the Secretary of HHS declares that there is a public health emergency that affects the national security or the health and security of United States citizens living abroad, and that involves biological agent(s) or a disease or condition that may be attributable to such agent(s). Criteria for issuing an EUA include:

- The biological agent(s) can cause a serious or life-threatening disease or condition;
- Based on the totality of the available scientific evidence (including data from adequate and well-controlled clinical trials, if available), it is reasonable to believe that
  - the product may be effective in diagnosing, treating, or preventing the serious or life-threatening disease or condition; and
  - the known and potential benefits of the product - when used to diagnose, prevent, or treat such disease or condition - outweigh the known and potential risks of the product, taking into consideration the material threat posed by the biological agent(s);
- There is no adequate, approved, and available alternative to the product for diagnosing, preventing, or treating the serious or life-threatening disease or condition.

CONTACT INFORMATION

If you have questions, please contact:

1-855-LillyC19 (1-855-545-5921)

For additional information visit:

www.baricitinibemergencyuse.com

END FACT SHEET

Revised 05/2022

Eli Lilly and Company, Indianapolis, IN 46285, USA

Copyright © 2020, 2022, Eli Lilly and Company. All rights reserved.

BAR-0005-EUA HCP-20220510

Fact Sheet for Patients, Parents and Caregivers
Emergency Use Authorization (EUA) of Baricitinib

You (or your child) are being given a medicine called baricitinib to treat coronavirus disease 2019 (COVID-19). This Fact Sheet contains information to help you understand the risks and benefits of taking baricitinib, which you (or your child) have received or may receive.

Taking baricitinib may benefit certain people in the hospital with COVID-19. This Fact Sheet provides you with the significant known and potential risks and benefits of the emergency use of baricitinib for treatment of COVID-19. Healthcare providers can recommend or provide baricitinib to people they believe may benefit from it as authorized.

Read this Fact Sheet for information about baricitinib and talk to your healthcare provider if you have questions. It is your choice to take baricitinib, have your child receive baricitinib, or stop it at any time.

What is COVID-19?

COVID-19 is caused by a virus called a coronavirus. You can get COVID-19 through contact with another person who has the virus. COVID-19 illnesses have ranged from very mild (including some with no reported symptoms) to severe, including illness resulting in death. While information so far suggests that most COVID-19 illness is mild, serious illness can happen and may cause some of your other medical conditions to become worse. People of all ages with severe, long-lasting (chronic) medical conditions like heart disease, lung disease, and diabetes, for example, seem to be at higher risk of being hospitalized for COVID-19.

What are the symptoms of COVID-19?

The symptoms of COVID-19 include fever, cough, and shortness of breath, which may appear 2 to 14 days after exposure. Serious illness including breathing problems can occur and may cause your other medical conditions to become worse.

What is baricitinib?

Baricitinib is a prescription medicine that is FDA approved to treat:

- adult patients with moderately to severely active rheumatoid arthritis after treatment with at least one other medicine called a Tumor Necrosis Factor (TNF) antagonist has been used and did not work well enough or could not be tolerated.
- COVID-19 in hospitalized adults requiring supplemental oxygen, non-invasive or invasive mechanical ventilation, or extracorporeal membrane oxygenation (ECMO).

Baricitinib is still being studied in hospitalized children with COVID-19. There is limited information about the safety and effectiveness of using baricitinib to treat children in the hospital with COVID-19.

The FDA has authorized the emergency use of baricitinib for the treatment of COVID-19 in children under an Emergency Use Authorization (EUA). For more information on EUA, see the section “What is an Emergency Use Authorization (EUA)?” at the end of this Fact Sheet.

What should I tell my healthcare provider before taking baricitinib (or before my child receives baricitinib)?

Tell your healthcare provider about all of your (or your child's) medical conditions, including if you (or your child):

- Have an infection other than COVID-19. You (or your child) should not take baricitinib if you have an active tuberculosis infection.
- Have hepatitis B, hepatitis C, or HIV.
- Have ever had any type of cancer.
- Have had blood clots.
- Have kidney problems. You (or your child) should not take baricitinib if you have sudden, severe kidney problems or you (or your child) are on dialysis.
- Have liver problems.
- Have low red or white blood cell counts.
- Have recently received a vaccine.
- Are pregnant or breastfeeding.
- Are allergic to baricitinib.

Tell your healthcare provider about all the medicines you (or your child) take, including prescription and over-the-counter medicines, vitamins, and herbal supplements.

Especially tell your healthcare provider if you (or your child) take:

- Probenecid
- Any medicines that affect your immune system

How should I (or my child) take baricitinib?

Baricitinib is given by mouth 1 time each day for 14 days or until you (or your child) are discharged from the hospital (whichever comes first), as instructed by your healthcare provider.

What are the important possible side effects of baricitinib?

Baricitinib may cause serious side effects, including:

- Serious infections. Baricitinib is a medicine that affects your (or your child's) immune system. Baricitinib can lower the ability of your (or your child's) immune system to fight infections other than COVID-19.
- Blood clots. Blood clots in the veins of your legs (deep vein thrombosis) or lungs (pulmonary embolism) can happen in some people taking baricitinib. This may be life threatening and cause death.
- Changes in certain laboratory test results. Your (or your child's) healthcare provider should do blood tests before you (or your child) start taking baricitinib to check how well your (or your child's) kidney and liver are working, as well as to check the number of white blood cells that help the body fight infections.
- Allergic reactions. Tell your (or your child's) healthcare provider right away if you (or your child) have symptoms such as rash, swelling of the lips, tongue, or throat, or hives (raised red patches of skin that are often very itchy). This may mean you (or your child) are having an allergic reaction.

For more information see the Medication Guide for Olumiant® (baricitinib), at http://pi.lilly.com/us/olumiant-us-mg.pdf.

Tell your (or your child's) healthcare provider immediately if you (or your child) get:

- swelling, pain or tenderness in the leg
- sudden unexplained chest pain
- sudden worsening shortness of breath
- rash, swelling of your lips, tongue, or throat, or hives

What other treatment choices are there?

Veklury (remdesivir) is FDA-approved for the treatment of certain adults and children who are hospitalized with COVID-19. Talk with your doctor to see if Veklury is appropriate for you.

Like baricitinib, FDA may allow for the emergency use of other medicines to treat people with COVID-19. Go to https://www.fda.gov/emergency-preparedness-andresponse/mcm-legal-regulatory-and-policy-framework/emergency-use-authorization for information on the emergency use of other medicines that are authorized by FDA to treat people with COVID-19. Your healthcare provider may talk with you about clinical trials for which you (or your child) may be eligible.

It is your choice for you (or your child) to be treated or not to be treated with baricitinib. Should you decide not to receive it or stop it at any time, it will not change your (or your child’s) standard medical care.

What if I am pregnant or breastfeeding?

Baricitinib has not been studied in pregnant women or breastfeeding mothers. It is not known if baricitinib will harm your unborn baby or if baricitinib passes into your breast milk. If you are pregnant or breastfeeding, discuss your options and specific situation with your healthcare provider.

How do I report side effects with baricitinib?

Tell your healthcare provider right away if you (or your child) have any side effect that bothers you (or them) or does not go away. Report side effects to FDA MedWatch at www.fda.gov/medwatch or call 1-800-FDA-1088. You may also report side effects to Lilly by calling 1-855-LillyC19 (1-855-545-5921).

How can I learn more?

- Ask your healthcare provider
- Visit https://www.cdc.gov/coronavirus/2019-ncov/index.html
- Contact your local or state public health department

What is an Emergency Use Authorization (EUA)?

The United States FDA has made baricitinib available under an emergency access mechanism called an Emergency Use Authorization (EUA). The EUA is supported by a Secretary of Health and Human Service (HHS) declaration that circumstances exist to justify the emergency use of drugs and biological products during the COVID-19 pandemic.

Baricitinib for treatment of COVID-19 in hospitalized pediatric patients 2 to less than 18 years of age requiring supplemental oxygen, non-invasive or invasive mechanical ventilation, or ECMO, has not undergone the same type of review as an FDA-approved product. In issuing an EUA under the COVID-19 public health emergency, the FDA has determined, among other things, that based on the total amount of scientific evidence available, including data from adequate and well-controlled clinical trials, if available, it is reasonable to believe that the product may be effective for diagnosing, treating, or preventing COVID-19, or a serious or life-threatening disease or condition caused by COVID-19; that the known and potential benefits of the product, when used to diagnose, treat, or prevent such disease or condition, outweigh the known and potential risks of such product; and that there are no adequate, approved and available alternatives.

All of these criteria must be met to allow for emergency use of the product during the COVID-19 pandemic. The EUA for baricitinib is in effect for the duration of the COVID-19 declaration justifying emergency use of baricitinib, unless terminated or revoked (after which baricitinib may no longer be used under the EUA).

Revised 05/2022

Eli Lilly and Company, Indianapolis, IN 46285, USA

Copyright © 2020, 2022, Eli Lilly and Company. All rights reserved.

BAR-0003-EUA PAT-20220510

PACKAGE LABEL – BARICITINIB 4 mg 30ct Bottle

Rx Only

NDC 0002-6885-30

baricitinib

tablets

4 mg

For use under Emergency Use Authorization (EUA).

30 tablets

Lilly